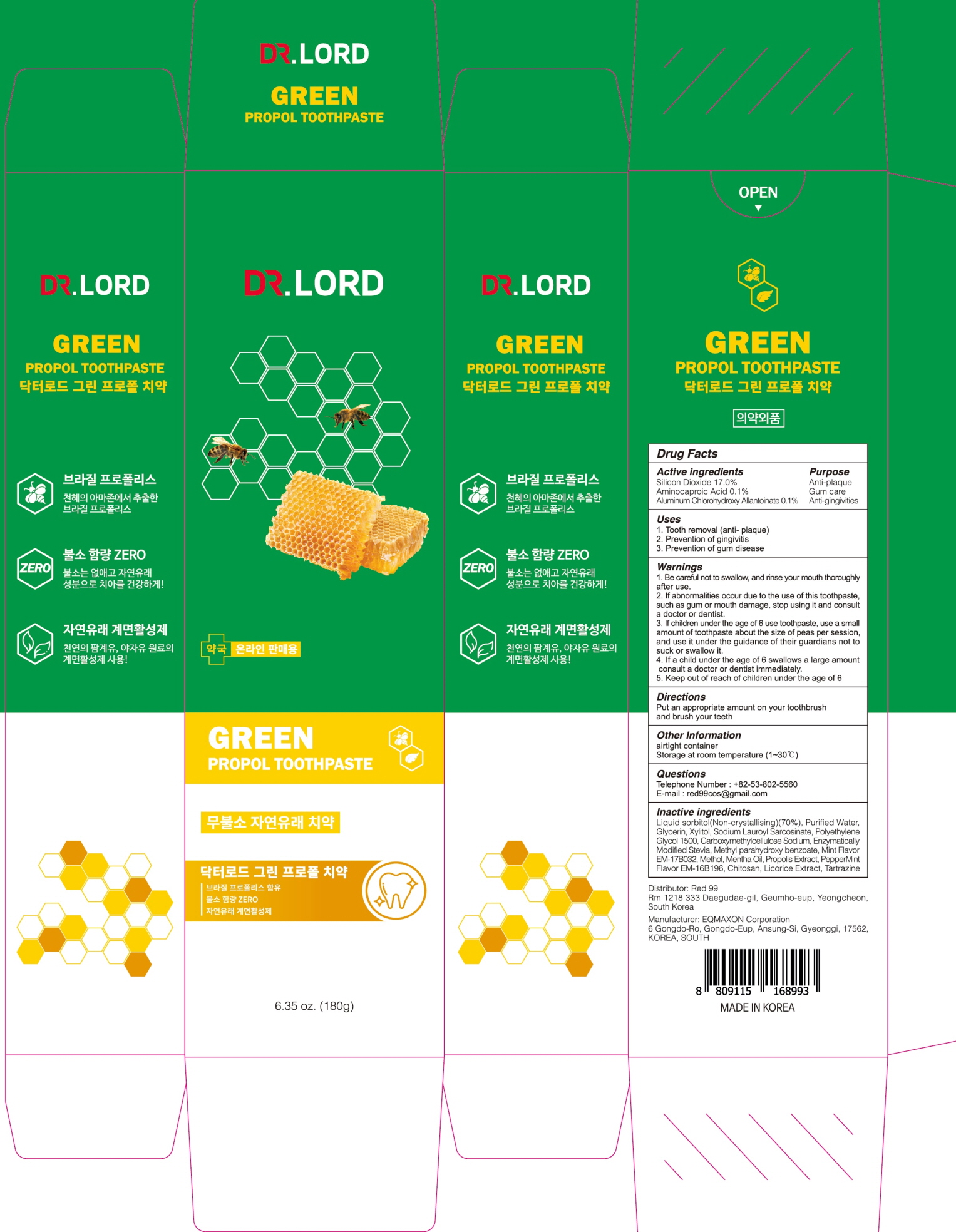 DRUG LABEL: Dr.LORD Green Propol Tooth
NDC: 82656-010 | Form: PASTE, DENTIFRICE
Manufacturer: Red 99
Category: otc | Type: HUMAN OTC DRUG LABEL
Date: 20220406

ACTIVE INGREDIENTS: Silicon Dioxide 17.0 g/100 g; Aminocaproic Acid 0.1 g/100 g; ALCLOXA 0.1 g/100 g
INACTIVE INGREDIENTS: Sorbitol; Water; Glycerin

ACTIVE INGREDIENTS

Silicon Dioxide 17.0%
Aminocaproic Acid 0.1%
Aluminum Chlorohydroxy Allantoinate 0.1%

INACTIVE INGREDIENTS

Liquid sorbitol(Non-crystallising)(70%), Purified Water, Glycerin, Xylitol, Sodium Lauroyl Sarcosinate, Polyethylene Glycol 1500, Carboxymethylcellulose Sodium, Enzymatically Modified Stevia, Methyl parahydroxy benzoate, Mint Flavor EM-17B032, Methol, Mentha Oil, Propolis Extract, PepperMint Flavor EM-16B196, Chitosan, Licorice Extract, Tartrazine

PURPOSE

Anti-plaque
Gum care
Anti-gingivities

WARNINGS

1. Be careful not to swallow, and rinse your mouth thoroughly after use.
2. If abnormalities occur due to the use of this toothpaste, such as gum or mouth damage, stop using it and consult a doctor or dentist.
3. If children under the age of 6 use toothpaste, use a small amount of toothpaste about the size of peas per session, and use it under the guidance of their guardians not to suck or swallow it.
4. If a child under the age of 6 swallows a large amount, consult a doctor or dentist immediately.
5. Keep out of reach of children under the age of 6

Keep out of reach of children under the age of 6

Uses

1. Tooth removal (anti- plaque)
2. Prevention of gingivitis
3. Prevention of gum disease

Directions

Put an appropriate amount on your toothbrush and brush your teeth.

Other Information

airtight container
Storage at room temperature (1~30℃)

Questions

Telephone Number : +82-53-802-5560
E-mail : red99cos@gmail.com